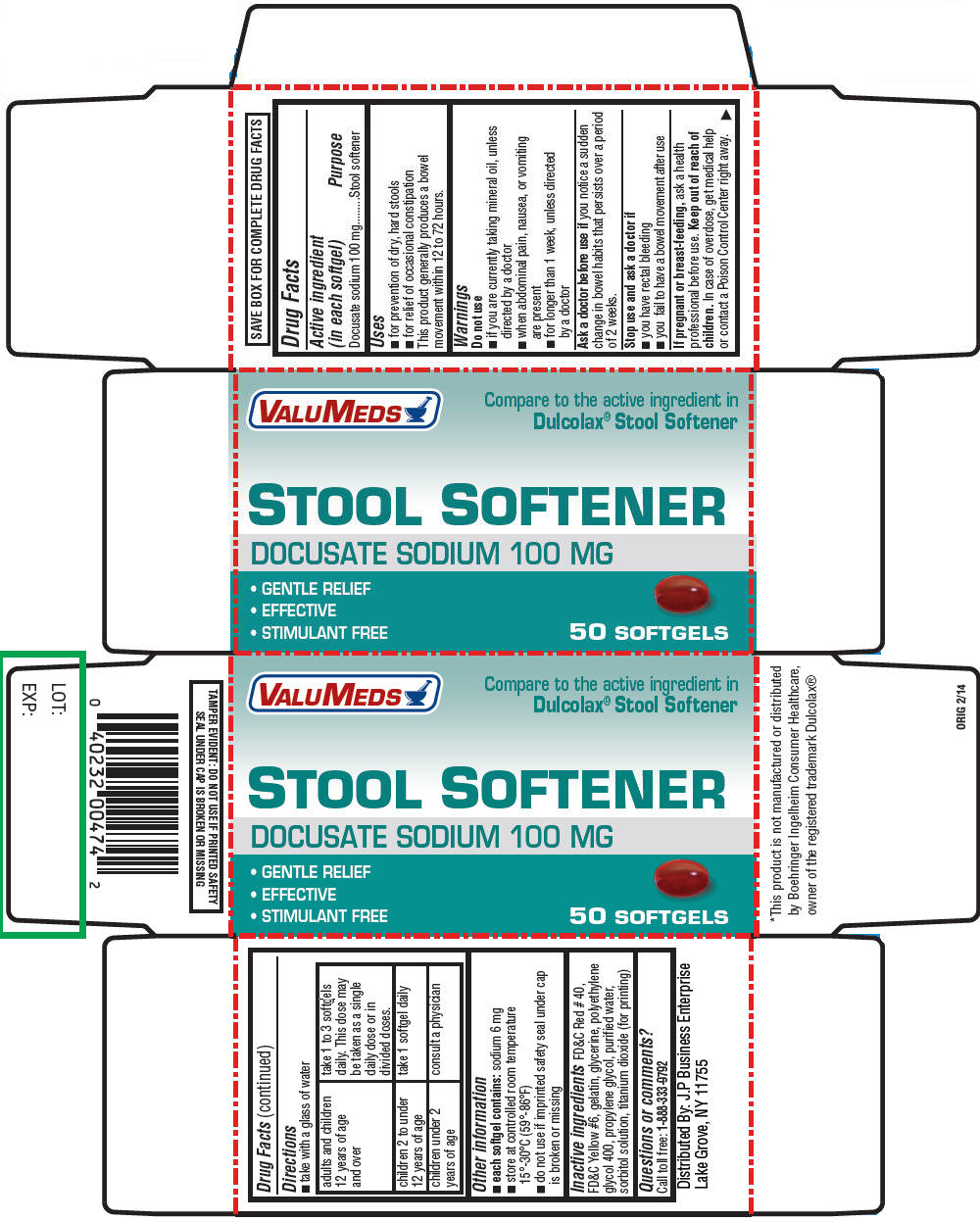 DRUG LABEL: DOCUSATE SODIUM
NDC: 59105-007 | Form: CAPSULE, LIQUID FILLED
Manufacturer: J.P. BUSINESS ENTERPRISE
Category: otc | Type: HUMAN OTC DRUG LABEL
Date: 20191226

ACTIVE INGREDIENTS: DOCUSATE SODIUM 100 mg/1 1
INACTIVE INGREDIENTS: POLYETHYLENE GLYCOL 400; PROPYLENE GLYCOL; GELATIN; GLYCERIN; SORBITOL; FD&C RED NO. 40; TITANIUM DIOXIDE; WATER

DOCUSATE SODIUM SOFTGEL CAPSULES 100MG

Drug Facts

Active ingredient (in each softgel)

Docusate sodium 100 mg

Purpose

Stool softener

Uses

- for prevention of dry, hard stools
- for relief of occasional constipation

This product generally produces a bowel movement within 12 to 72 hours.

Warnings

Do not use

- if you are currently taking mineral oil, unless directed by a doctor
- when abdominal pain, nausea, or vomiting are present
- for longer than 1 week, unless directed by a doctor

Ask a doctor before use if you notice a sudden change in bowel habits that persists over a period of 2 weeks.

Stop use and ask a doctor if

- you have rectal bleeding
- you fail to have a bowel movement after use

PREGNANCY OR BREAST FEEDING

If pregnant or breast-feeding, ask a health professional before use.

Keep out of reach of children. In case of overdose, get medical help or contact a Poison Control Center right away.

Directions

- take with a glass of water

adults and children 12 years of age and over | take 1 to 3 softgels daily. This dose may be taken as a single daily dose or in divided doses.
children 2 to under 12 years of age | take 1 softgel daily
children under 2 years of age | consult a physician

Other information

- each softgel contains: sodium 6 mg
- store at controlled room temperature 15°-30°C (59°-86°F)
- do not use if imprinted safety seal under cap is broken or missing

Inactive ingredients

FD&C Red # 40, FD&C Yellow #6, gelatin, glycerine, polyethylene glycol 400, propylene glycol, purified water, sorbitol solution, titanium dioxide (for printing)

Questions or comments?

Call toll free: 1-888-333-9792

Distributed By: J.P Business Enterprise
Lake Grove, NY 11755

PRINCIPAL DISPLAY PANEL - 50 Softgel Bottle Carton

VALUMEDS

Compare to the active ingredient in
Dulcolax® Stool Softener

STOOL SOFTENER
DOCUSATE SODIUM 100 MG

- GENTLE RELIEF
- EFFECTIVE
- STIMULANT FREE

50 SOFTGELS